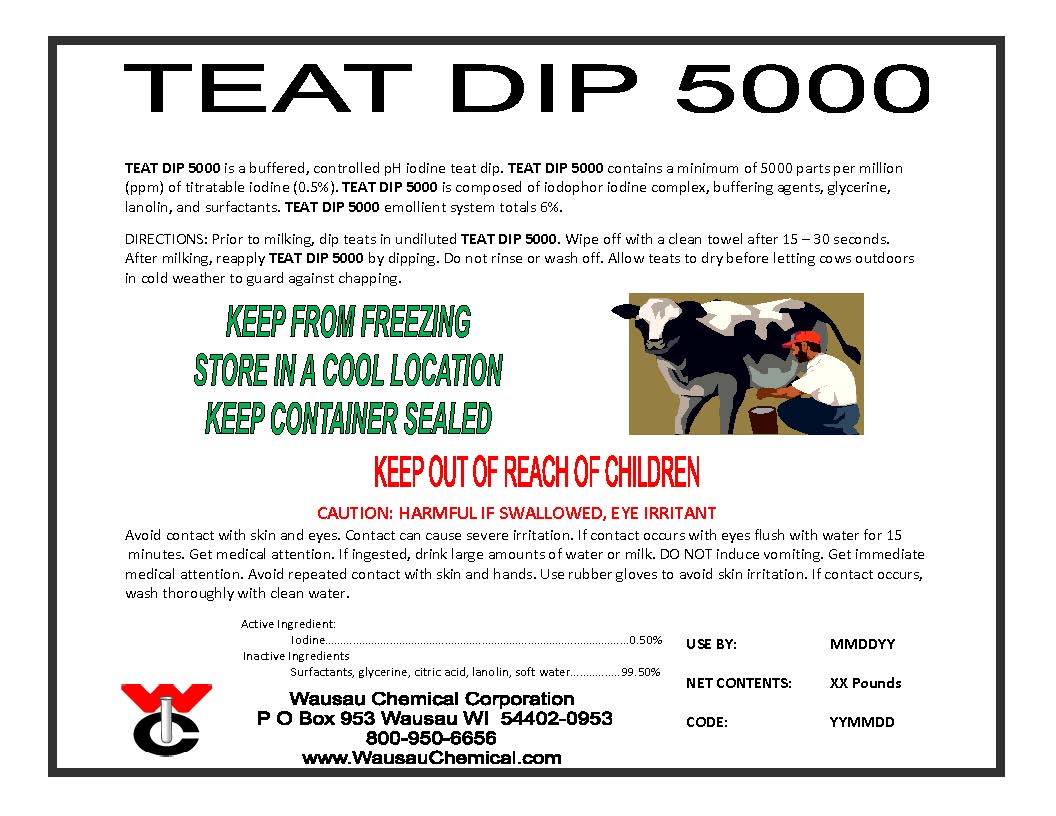 DRUG LABEL: Teat Dip 5000
NDC: 64892-002 | Form: SOLUTION
Manufacturer: Wausau Chemical
Category: animal | Type: OTC ANIMAL DRUG LABEL
Date: 20120529

ACTIVE INGREDIENTS: IODINE 0.5 L/100 L

GENERAL PRECAUTIONS

FOR COMMERCIAL USE ONLY

KEEP OUT OF REACH OF CHILDREN

NOT FOR HUMAN USE

CAUTION

Harmful if swallowed, eye irritant.

FIRST AID:

Avoid contact with skin and eyes. Contact can cause severe irritation. If contact occurs with eyes flush with water for 15 minutes. Get medical attention. If ingested, drink large amounts of water or milk. DO NOT induce vomiting.

Get immediate medical attention. Avoid repeated contact with skin and hands. Use rubber gloves to avoid skin irritation. If contact occurs, wash thoroughly with clean water.

EMERGENCY: CHEMTREC 800-424-9300

Directions:

Prior to milking, dip teats in undiluted Teat Dip 5000. Wipe off with a clean towel after 15 to 30 seconds.

After milking, reapply Teat Dip 5000 by dipping. Do not rinse or wash off. Allow teats to dry before letting cows

outdoors in cold weather to guard against chapping.

PACKAGE LABEL

Teat Dip 5000
Iodine Teat Dip
An aid in Reducing the Spread of Organisms
Which May Cause Mastitis
ACTIVE INGREDIENTS:
Iodine..................................................0.5%
INACTIVE INGREDIENTS....................99.5%